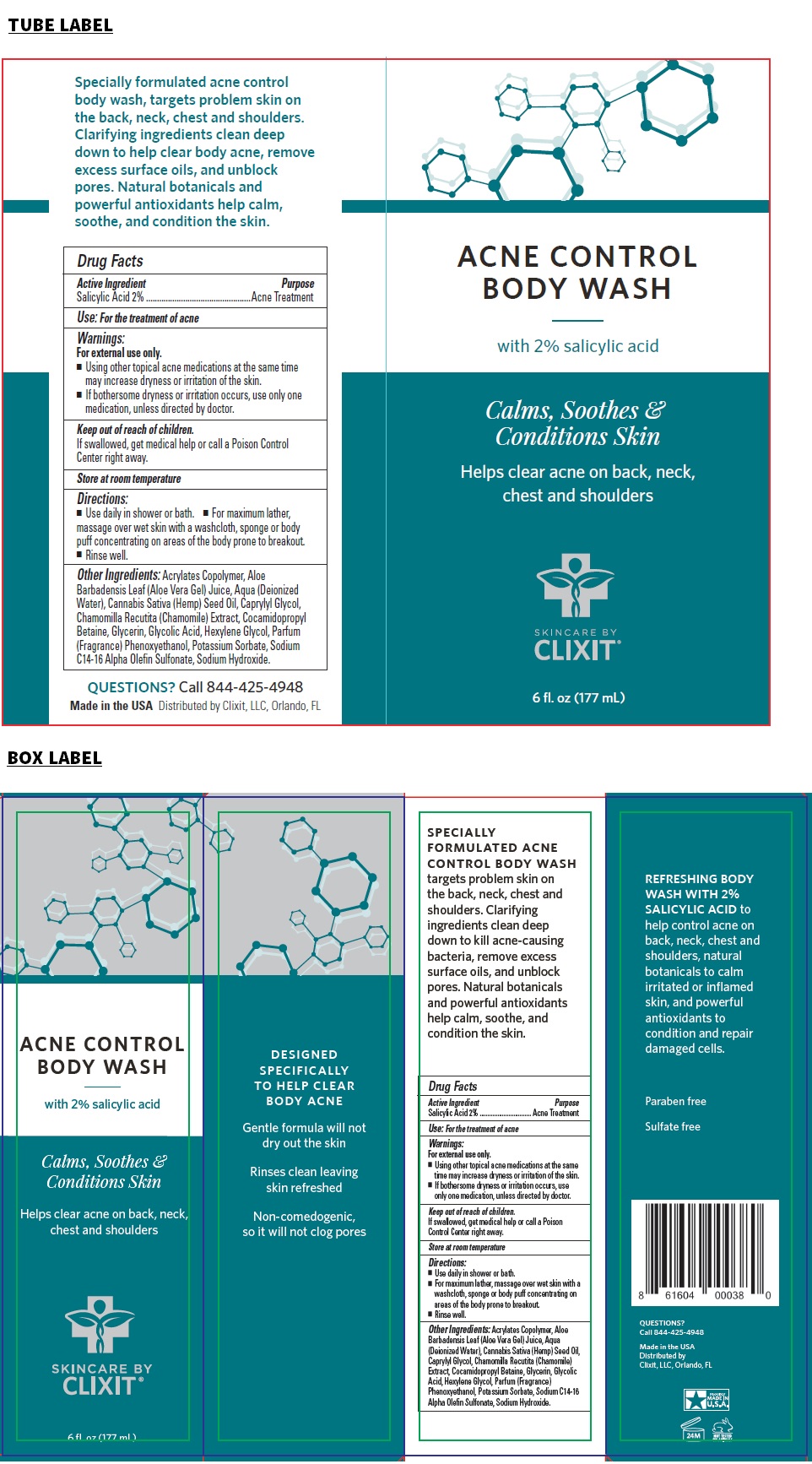 DRUG LABEL: CLIXIT ACNE CONTROL BODY WASH
NDC: 71328-043 | Form: GEL
Manufacturer: Clixit, Llc
Category: otc | Type: HUMAN OTC DRUG LABEL
Date: 20210417

ACTIVE INGREDIENTS: SALICYLIC ACID 20 mg/1 mL
INACTIVE INGREDIENTS: METHACRYLIC ACID AND ETHYL ACRYLATE COPOLYMER; ALOE VERA LEAF; WATER; CANNABIS SATIVA SEED OIL; CAPRYLYL GLYCOL; CHAMOMILE; COCAMIDOPROPYL BETAINE; GLYCERIN; GLYCOLIC ACID; HEXYLENE GLYCOL; PHENOXYETHANOL; POTASSIUM SORBATE; SODIUM C14-18 OLEFIN SULFONATE; SODIUM HYDROXIDE

CLIXIT® ACNE CONTROL BODY WASH

Active Ingredient

Salicylic Acid 2%

Purpose

Acne Treatment

Use:

For the treatment of acne

Warnings:

For external use only.
• Using other topical acne medications at the same time may increase dryness or irritation of the skin.
• If bothersome dryness or irritation occurs, use only one medication, unless directed by doctor.

Store at room temperature

Keep out of reach of children.
If swallowed, get medical help or call a Poison Control Center right away.

Directions:

• Use daily in shower or bath.
• For maximum lather, massage over wet skin with a washcloth, sponge or body puff concentrating on areas of the body prone to breakout.
• Rinse well.

Other Ingredients:

Acrylates Copolymer, Aloe Barbadensis Leaf (Aloe Vera Gel) Juice, Aqua (Deionized Water), Cannabis Sativa (Hemp) Seed Oil, Caprylyl Glycol, Chamomilla Recutita (Chamomile) Extract, Cocamidopropyl Betaine, Glycerin, Glycolic Acid, Hexylene Glycol, Parfum (Fragrance), Phenoxyethanol, Potassium Sorbate, Sodium C14-16 Alpha Olefin Sulfonate, Sodium Hydroxide.

Calms, Soothes & Conditions Skin

Helps clear acne on back, neck, chest and shoulders

SKINCARE BY CLIXIT®

DESIGNED SPECIFICALLY TO HELP CLEAR BODY ACNE

Gentle formula will not dry out the skin

Rinses clean leaving skin refreshed

Non-comedogenic, so it will not clog pores

SPECIALLY FORMULATED ACNE CONTROL BODY WASH targets problem skin on the back, neck, chest and shoulders. Clarifying ingredients clean deep down to kill acne-causing bacteria, remove excess surface oils, and unblock pores. Natural botanicals and powerful antioxidants help calm, soothe, and condition the skin.

REFRESHING BODY WASH WITH 2% SALICYLIC ACID to help control acne on back, neck, chest and shoulders, natural botanicals to calm irritated or inflamed skin, and powerful antioxidants to condition and repair damaged cells.

Paraben free

Sulfate free

QUESTIONS?
Call 844-425-4948

Made in the USA
Distributed by
Clixit, LLC, Orlando, FL

NOT TESTED ON ANIMALS